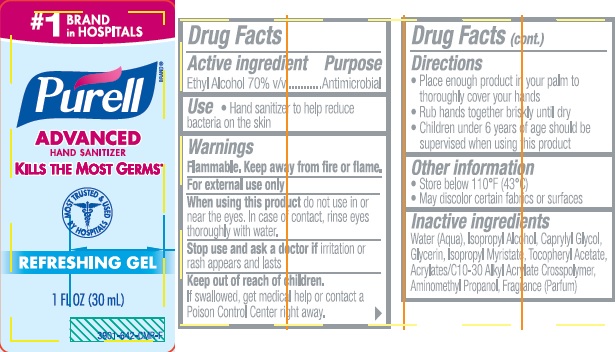 DRUG LABEL: Purell Advanced Refreshing
NDC: 21749-704 | Form: GEL
Manufacturer: GOJO Industries, Inc.
Category: otc | Type: HUMAN OTC DRUG LABEL
Date: 20260112

ACTIVE INGREDIENTS: ALCOHOL 70 mL/100 mL
INACTIVE INGREDIENTS: WATER; ISOPROPYL ALCOHOL; CAPRYLYL GLYCOL; GLYCERIN; ISOPROPYL MYRISTATE; .ALPHA.-TOCOPHEROL ACETATE, D-; AMINOMETHYLPROPANOL

PURELL Advanced Hand Sanitizer Refreshing Gel

Active ingredient

Ethyl alcohol 70% v/v

Purpose

Antimicrobial

Uses

- Hand sanitizer to help reduce bacteria on the skin

Warnings

Flammable. Keep away from fire or flame.

For external use only

When using this product do not use in or near the eyes. In case of contact, rinse eyes thoroughly with water.

Stop use and ask a doctor if irritation or rash appears and lasts

Keep Out of Reach of Children. If swallowed, get medical help or contact a Poison Control Center right away.

Directions

- Put enough product in your palm to cover hands and rub hands together briskly until dry
- Children under 6 years of age should be supervised when using PURELL

Inactive ingredients

Water (Aqua), Isopropyl Alcohol, Caprylyl Glycol, Glycerin, Isopropyl Myristate, Tocopheryl Acetate, Acrylates/C10-30 Alkyl Acrylate Crosspolymer, Aminomethyl Propanol, Fragrance (Parfum)